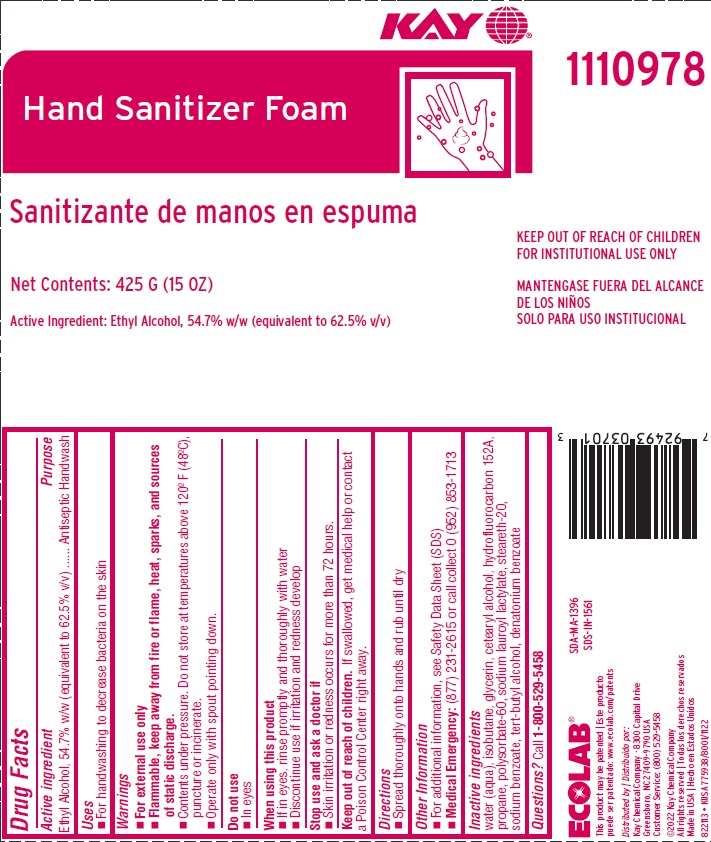 DRUG LABEL: Kay Hand Sanitizer Foam
NDC: 47593-683 | Form: SOLUTION
Manufacturer: Ecolab Inc.
Category: otc | Type: HUMAN OTC DRUG LABEL
Date: 20251217

ACTIVE INGREDIENTS: ALCOHOL 54.7 g/100 g
INACTIVE INGREDIENTS: Water; isobutane; GLYCERIN; 1,1-DIFLUOROETHANE; CETOSTEARYL ALCOHOL; POLYSORBATE 60; PROPANE; SODIUM LAUROYL LACTYLATE; STEARETH-20; SODIUM BENZOATE; TERT-BUTYL ALCOHOL; DENATONIUM BENZOATE

Drug Facts

Active Ingredient

Ethyl alcohol 54.7 w/w (equivalent to 62.5% v/v)

Purpose

Antiseptic Handwash

Uses

- For handwashing to decrease bacteria on the skin

Warnings

- For external use only
- Flammable, keep away from fire or flame, heat, sparks and sources of static discharge.
- Contents under pressure. Do not store at temperatures above 120°F (48°C), puncture or incinerate
- Operate only with spout pointing down

Do not use

- In eyes

When using this product

- If in eyes, rinse promptly and thoroughly with water
- Discontinue use if irritation and redness develop

Stop use and ask a doctor if skin irritation or redness develop occurs for more than 72 hours

Keep out of reach of children. If swallowed, get medical help or contact a Poison Control Center right away

Directions

- Spread thoroughly onto hands and rub until dry

Other Information

- for additional information, see Safety Data Sheet (SDS)
- Medical Emergency: (877) 231-2615 or call collect 0 (952) 853-1713

INACTIVE INGREDIENT

Inactive Ingredients water (aqua), isobutane, glycerin, cetearyl alcohol, hydrofluorocarbon 152A, propane, polysorbate-60, sodium lauroyl lactylate, steareth-20, sodium benzoate, tert-butyl alcohol, denatonium benzoate

Questions? Call 1-800-529-5458

Representative Label and Principal Display Panel

KAY®

Hand Sanitizer Foam

Net Contents: 425 g (15 oz)

Active Ingredient: 54.7% w/w (equivalent to 62.5% v/v)

1110978

ECOLAB

This product may be patented | Este producto

puede ser patentado: www.ecolab.com/patents

Distributed by | Distribuido por:

Kay Chemical Company · 8300 Capital Drive

Greensboro, NC 27409-9790 USA

Customer Service: (800) 529-5458

©2022 Kay Chemical Company

All rights reserved | Todas los derechos reservados

Made in USA | Hecho en Estados Unidos

822113 • KUSA 775938/8001/1122